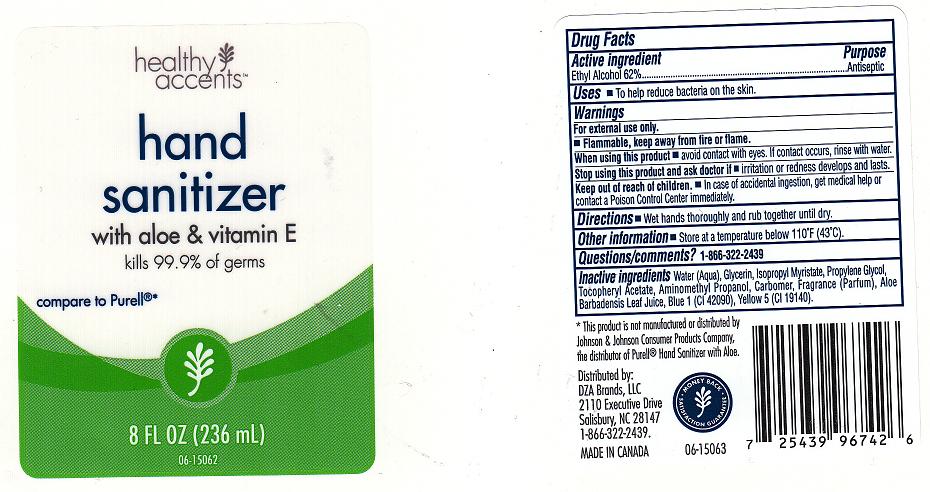 DRUG LABEL:  HAND SANITIZER
NDC: 55316-223 | Form: GEL
Manufacturer: DZA BRANDS LLC
Category: otc | Type: HUMAN OTC DRUG LABEL
Date: 20110623

ACTIVE INGREDIENTS: ALCOHOL 62 mL/100 mL
INACTIVE INGREDIENTS: WATER; GLYCERIN; ISOPROPYL MYRISTATE; CARBOMER 934; AMINOMETHYLPROPANOL; PROPYLENE GLYCOL; ALPHA-TOCOPHEROL ACETATE; ALOE VERA LEAF; FD&C BLUE NO. 1; FD&C YELLOW NO. 5

DRUG FACTS

ACTIVE INGREDIENT

ETHYL ALCOHOL 65%

PURPOSE

ANTISEPTIC

USES

TO HELP REDUCE BACTERIA ON THE SKIN.

WARNINGS

FOR EXTERNAL USE ONLY. FLAMMABLE, KEEP AWAY FROM FIRE OR FLAME.

WHEN USING THIS PRODUCT

AVOID CONTACT WITH EYES. IF CONTACT OCCURS, RINSE WITH WATER.

STOP USING THIS PRODUCT AND ASK DOCTOR IF

IRRITATION OR REDNESS DEVELOPS AND LASTS.

KEEP OUT OF REACH OF CHILDREN

IN CASE OF ACCIDENTAL INGESTION, GET MEDICAL HELP OR CONTACT A POISON CONTROL CENTER IMMEDIATELY.

DIRECTIONS

WET HANDS THOROUGHLY AND RUB TOGETHER UNTIL DRY.

OTHER INFORMATION

STORE AT A TEMPERATURE BELOW 110 DEGREES FAHRENHEIT (43 DEGREES CELSIUS).

QUESTIONS AND COMMENTS

1-866-322-2439

INACTIVE INGREDIENTS

WATER, GLYCERIN, ISOPROPYL MYRISTATE, PROPYLENE GLYCOL, TOCOPHERYL ACETATE, AMINOMETHYL PROPANOL, CARBOMER, FRAGRANCE, ALOE BARBADENSIS LEAF JUICE, BLUE 1 (CI 42090), YELLOW 5 (CI 19140).